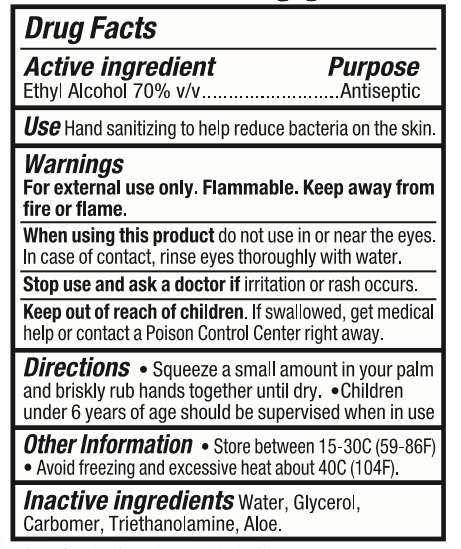 DRUG LABEL: HAND SANITIZER
NDC: 77720-006 | Form: GEL
Manufacturer: Skaffles Group Limited Liability Company
Category: otc | Type: HUMAN OTC DRUG LABEL
Date: 20200706

ACTIVE INGREDIENTS: ALCOHOL 70 mL/100 mL
INACTIVE INGREDIENTS: GLYCERIN; CARBOMER HOMOPOLYMER, UNSPECIFIED TYPE; WATER; TROLAMINE; ALOE VERA LEAF

77720-006 HAND SANITIZER 70% Ethyl Alcohol

Active Ingredient

Ethyl Alcohol 70%

Purpose

Antiseptic

USE

Hand sanitizing to help reduce bacteria on the skin.

Warning

For external use only. Flammable. Keep away from
When using this product do not use in or near the eyes.
In case of contact, rinse eyes thoroughly with water.
Stop use and ask a doctor if irritation or rash occurs.

Keep out of reach of children. If swallowed, get medical
help or contact a Poison Control Center right away.

Directions

Squeeze a small amount in your palm
and briskly rub hands together until dry. Children
under 6 years of age should be supervised when in use

Inactive ingredients

Water, Glycerol,Carbomer, Triethanolamine, Aloe.